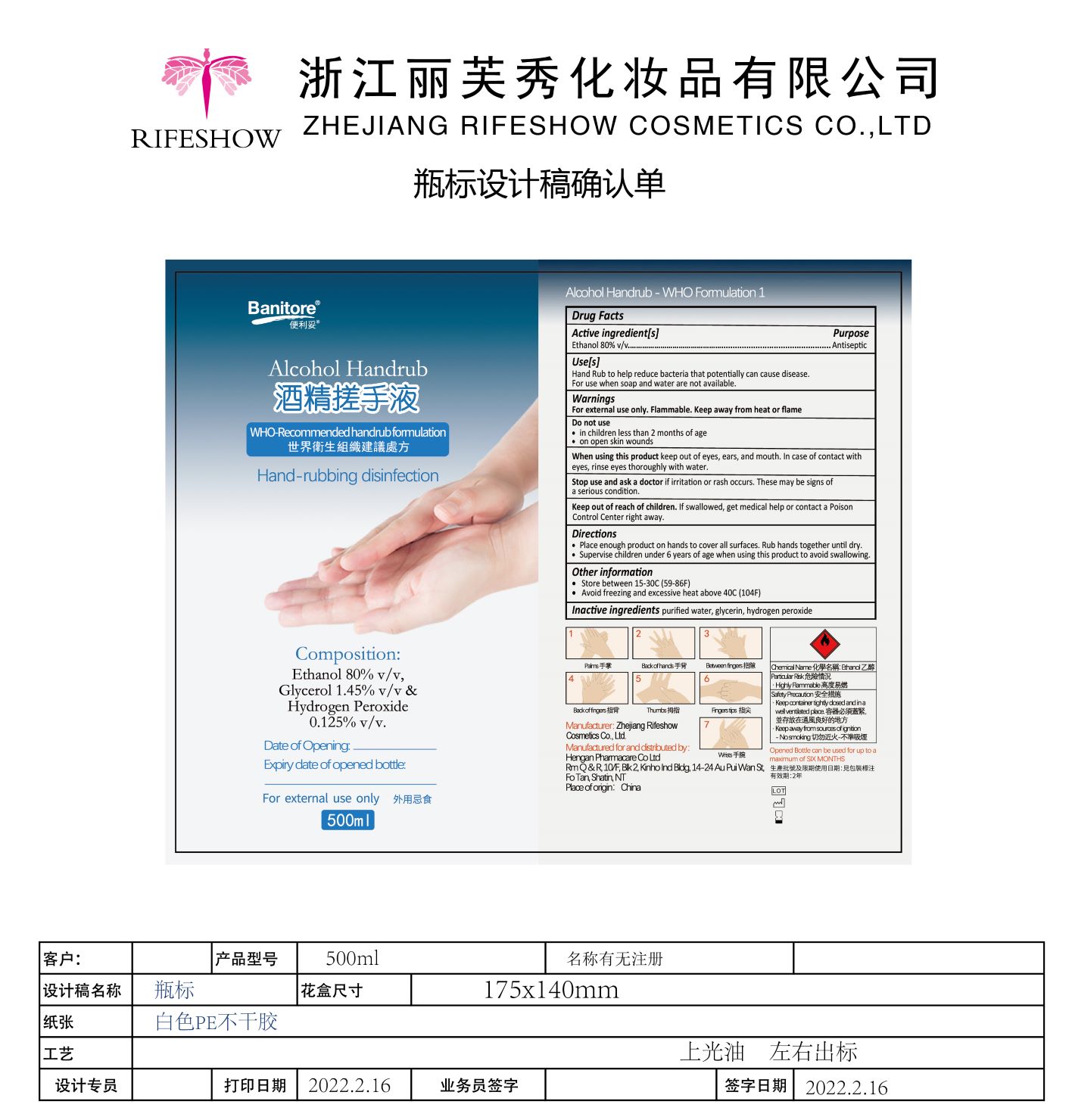 DRUG LABEL: BANITORE Alcohol Hand Rub
NDC: 56084-031 | Form: LIQUID
Manufacturer: Zhejiang RIFESHOW Cosmetics Co., Ltd.
Category: otc | Type: HUMAN OTC DRUG LABEL
Date: 20220309

ACTIVE INGREDIENTS: ALCOHOL 80 mL/100 mL
INACTIVE INGREDIENTS: WATER; GLYCERIN; HYDROGEN PEROXIDE

Zhejiang RIFESHOW Cosmetics Co., Ltd.
Alcohol Hand Rub
500ml 56084-029-01

Active Ingredient(s)

Ethanol 80% v/v

Purpose

Antiseptic

Use

- Hand Rub to help reduce bacteria that potentially can cause disease.
- For use when soap and water are not available.

Warnings

- For external use only.
- Flammable. Keep away from heat or flame.

Stop use and ask a doctor if irritation or rash occurs. These may be signs of a serious condition.

Do not use

- in children less than 2 months of age.
- on open skin wounds.

Directions

- Place enough product on hands to cover all surfaces. Rub hands together until dry.
- Supervise children under 6 years of age when using this product to avoid swallowing.

Keep out of reach of children. If swallowed, get medical help or contact a Poison Control Center right away.

Other information

- Store between 15-30℃（59-86℉）.
- Avoid freezing and excessive heat above 40℃（104℉）.

Inactive ingredients

purified water, glycerin, hydrogen peroxide.

When using this product keep out of eyes, ears, and mouth. In case of contact with eyes, rinse eyes througthly with water.

Package Label - Principal Display Panel

500mL NDC: 56084-031-01